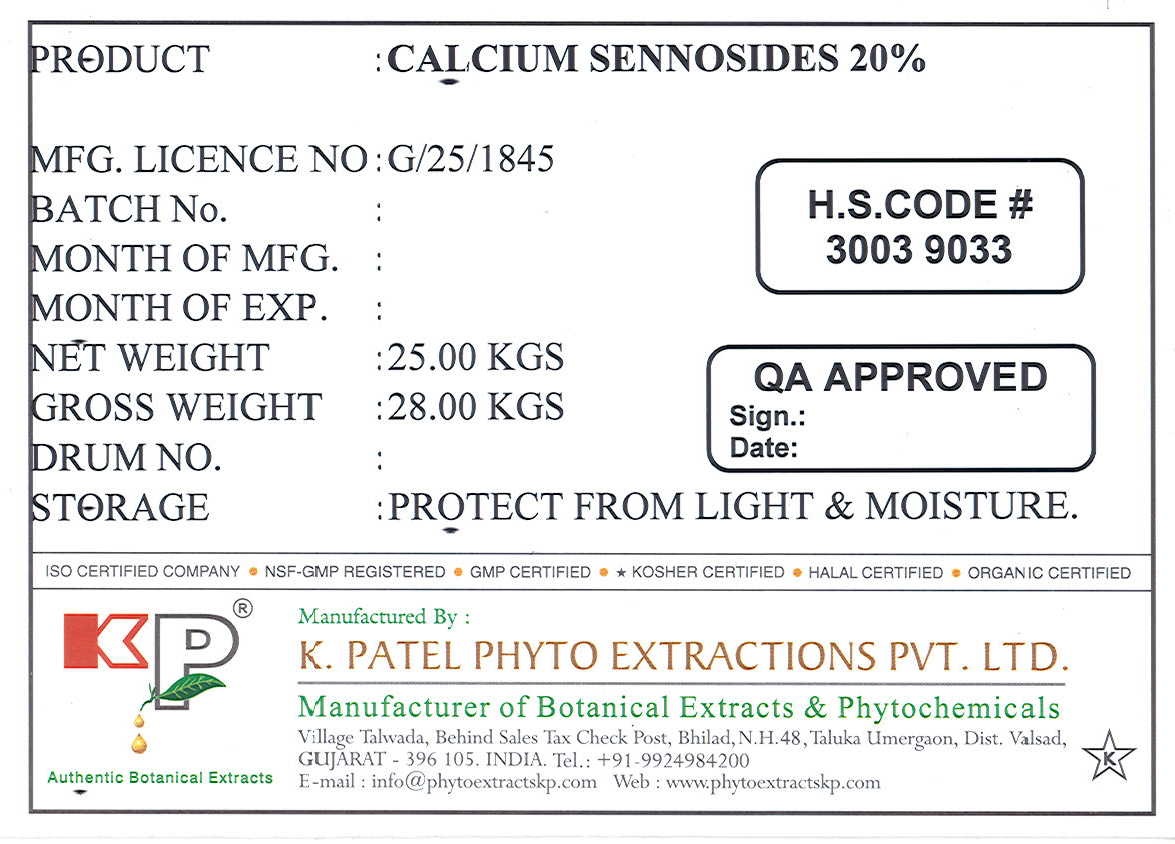 DRUG LABEL: Calcium Sennosides
NDC: 73276-001 | Form: POWDER
Manufacturer: K. Patel Phyto Extractions Private Limited
Category: other | Type: BULK INGREDIENT
Date: 20230109

ACTIVE INGREDIENTS: SENNOSIDES 25 kg/25 kg

Calcium Sennosides 20 %